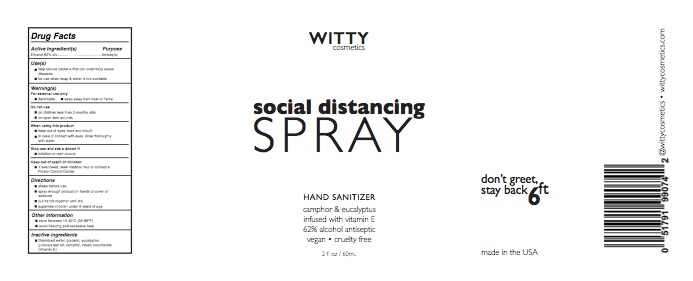 DRUG LABEL: Hand Sanitizer
NDC: 78276-223 | Form: LIQUID
Manufacturer: Witty Cosmetics
Category: otc | Type: HUMAN OTC DRUG LABEL
Date: 20200526

ACTIVE INGREDIENTS: ALCOHOL 620 mL/1000 mL
INACTIVE INGREDIENTS: WATER

SDSpart 2

ACTIVE INGREDIENT

Ethanol 62% vlv............................................Antiseptic

INDICATIONS AND USAGE

- help reduce bacteria that can potentially cause diseases
- for use when soap & water is not available

WARNINGS

- For external use only
- flammable keep away from heat or flame
- Do not use on children less than 2 months olds on open skin wounds
- When using this product keep out of eyes, ears and mouth
- in case of contact with eyes, rinse thoroughly with water
- Stop use and ask a doctor if irritation or rash occurs

Keep out of reach of children

- If swallowed, seek medical help or contact a Poison Control Center.

INACTIVE INGREDIENT

- Deionized water, glycerin, eucalyptus globulus leaf oil, camphor, mixed tocopherols (Vitamin E)

DOSAGE AND ADMINISTRATION

2 fl oz (60ml)

PURPOSE

- help reduce bacteria that can potentially cause diseases
- for use when soap & water is not available

PACKAGE LABEL

620ml NDC: 78276-223-92